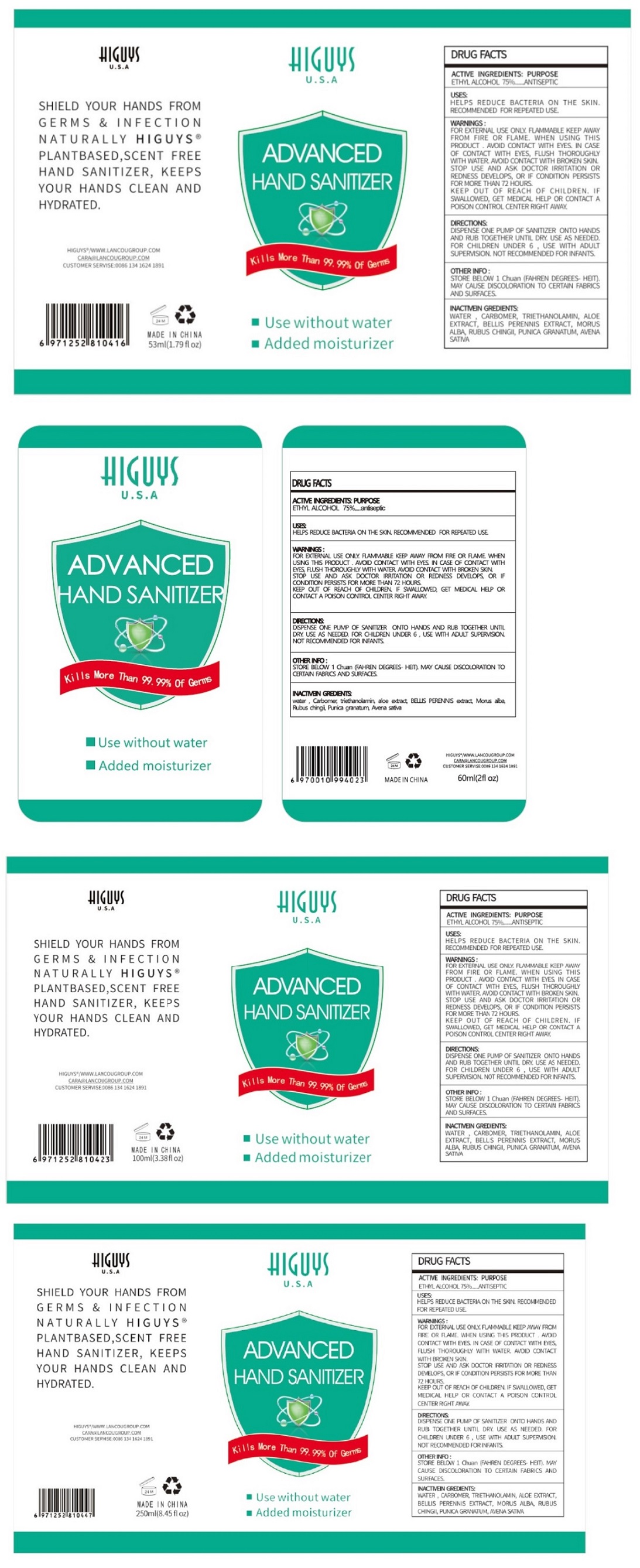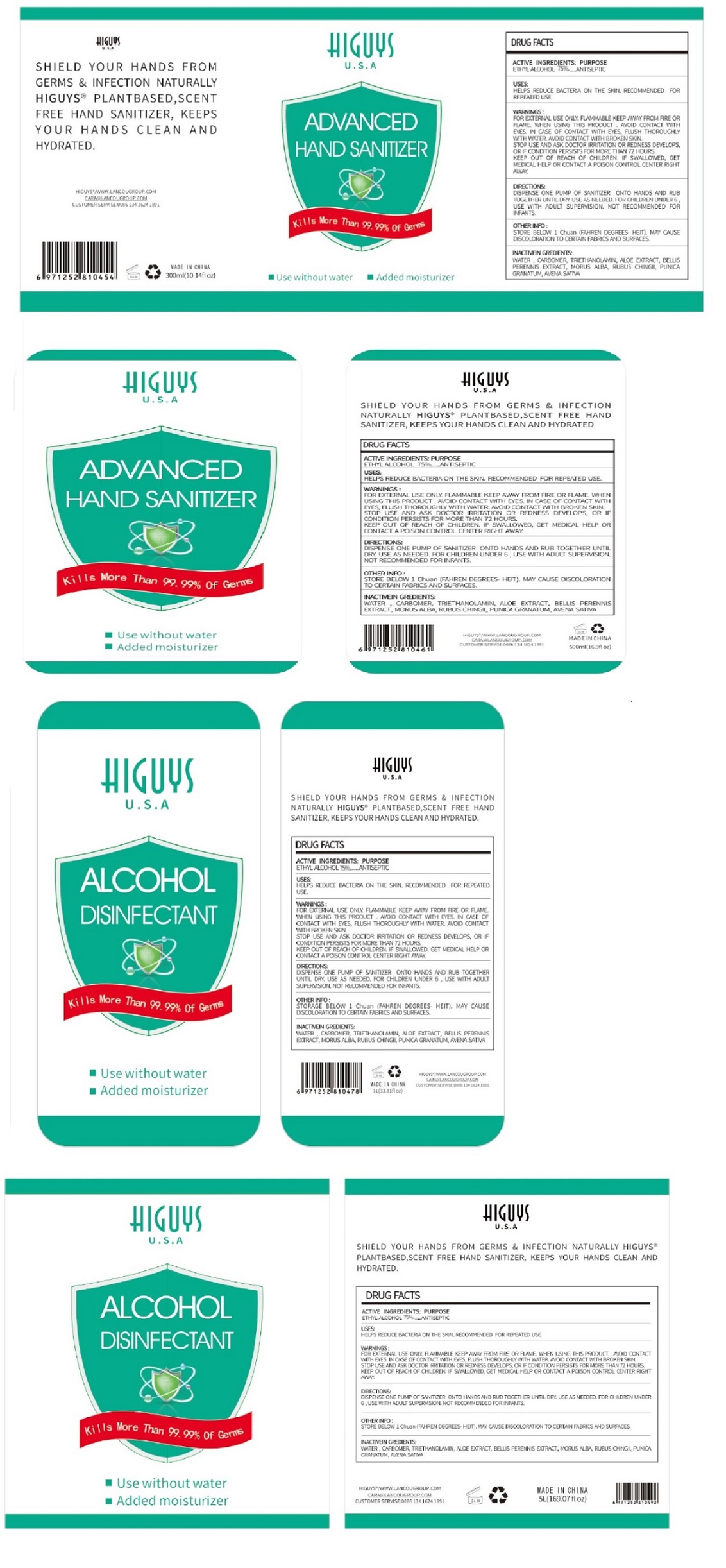 DRUG LABEL: HIGUYS
NDC: 74416-170 | Form: LIQUID
Manufacturer: Guangzhou C-kang Biotechnology Co., Ltd.
Category: otc | Type: HUMAN OTC DRUG LABEL
Date: 20200528

ACTIVE INGREDIENTS: ALCOHOL 75 mL/100 mL
INACTIVE INGREDIENTS: WATER; CARBOMER HOMOPOLYMER, UNSPECIFIED TYPE; TROLAMINE; ALOE; BELLIS PERENNIS WHOLE; MORUS ALBA WHOLE; RUBUS CHINGII WHOLE; PUNICA GRANATUM WHOLE; AVENA SATIVA FLOWERING TOP

HIGUYS U.S.A ADVANCED HAND SANITIZER

ACTIVE INGREDIENTS:

ETHYL ALCOHOL 75%

PURPOSE

ANTISEPTIC

USES:

HELPS REDUCE BACTERIA ON THE SKIN. RECOMMENDED FOR REPEATED USE.

WARNINGS:

FOR EXTERNAL USE ONLY. FLAMMABLE. KEEP AWAY FROM FIRE OR FLAME. WHEN USING THIS PRODUCT. AVOID CONTACT WITH EYES, IN CASE OF CONTACT WITH EYES, FLUSH THOROUGHLY WITH WATER. AVOID CONTACT WITH BROKEN SKIN. STOP USE AND ASK DOCTOR IRRITATION OR REDNESS DEVELOPS, OR IF CONDITION PERSISTS FOR MORE THAN 72 HOURS.

KEEP OUT OF REACH OF CHILDREN. IF SWALLOWED, GET MEDICAL HELP OR CONTACT A POISON CONTROL CENTER RIGHT AWAY.

DIRECTIONS:

DISPENSE ONE PUMP OF SANITIZER ONTO HANDS AND RUB TOGETHER UNTIL DRY. USE AS NEEDED. FOR CHILDREN UNDER 6, USE WITH ADULT SUPERVISION. NOT RECOMMENDED FOR INFANTS.

OTHER INFO:

STORE BELOW 1 Chuan (FAHREN DEGREES- HEIT). MAY CAUSE DISCOLORATION TO CERYAIN FABRICS AND SURFACES.

INACTIVE INGREDIENTS:

WATER, CARBOMER, TRIETHANOLAMIN, ALOE EXTRACT, BELLIS PERENNIS EXTRACT, MORUS ALBA, RUBUS CHINGII, PUNICA GRANATUM, AVENA SATIVA

Kills More Than 99.99% Of Germs

■ Use without water

■ Added moisturizer

SHIELD YOUR HANDS FROM GERMS & INFECTION NAYURALLY HIGUYS® PLANTBASED, SCENT FREE HAND SANITIZER, KEEPS YOUR HANDS CLEAN AND HYDRATED.

HIGUYS®/WWW.LANCOUGROUP.COM

CARA@LANCOUGROUP.COM

CUSTOMER SERVICE: 0086 134 1624 1891

MADE IN CHINA